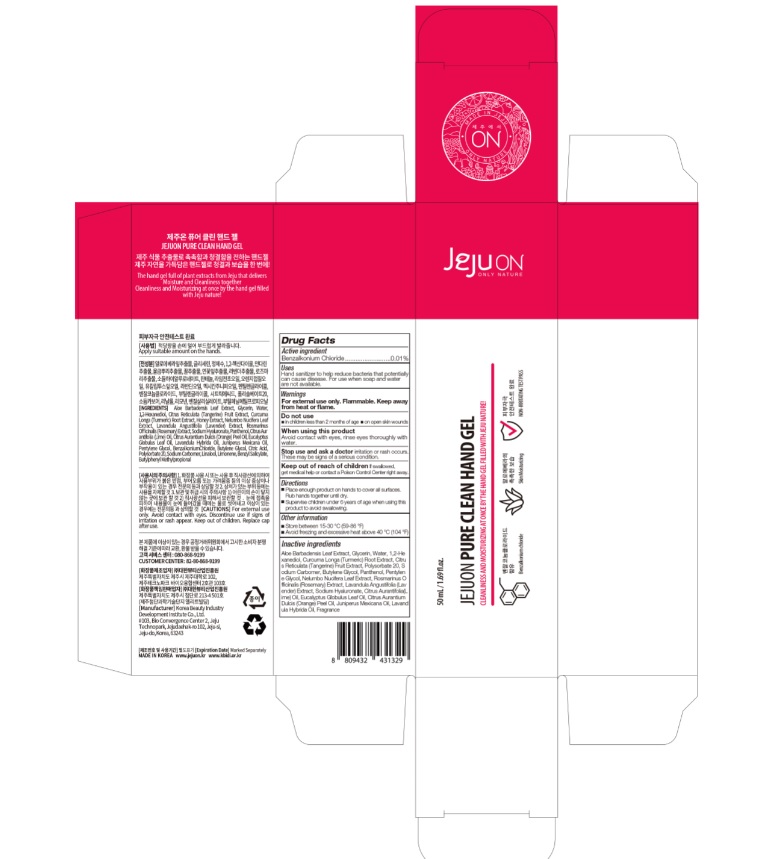 DRUG LABEL: JEJUON Pure Clean Hand Gel
NDC: 76744-250 | Form: GEL
Manufacturer: Korea Beauty Industry Development Institute Co.,Ltd.
Category: otc | Type: HUMAN OTC DRUG LABEL
Date: 20200508

ACTIVE INGREDIENTS: BENZALKONIUM CHLORIDE 0.5 g/50 mL
INACTIVE INGREDIENTS: ALOE VERA LEAF; TANGERINE; GLYCERIN; HONEY; EUCALYPTUS OIL; LAVANDIN OIL; CITRIC ACID MONOHYDRATE; POLYSORBATE 20; SODIUM CARBONATE; NELUMBO NUCIFERA LEAF; TURMERIC; PANTHENOL; ORANGE OIL; BUTYLENE GLYCOL; LAVANDULA ANGUSTIFOLIA FLOWERING TOP; ROSEMARY; LIME OIL; JUNIPERUS DEPPEANA WOOD OIL; PENTYLENE GLYCOL; WATER; 1,2-HEXANEDIOL; HYALURONATE SODIUM

JEJUON Pure Clean Hand Gel: Tube < Box :76744-250-02